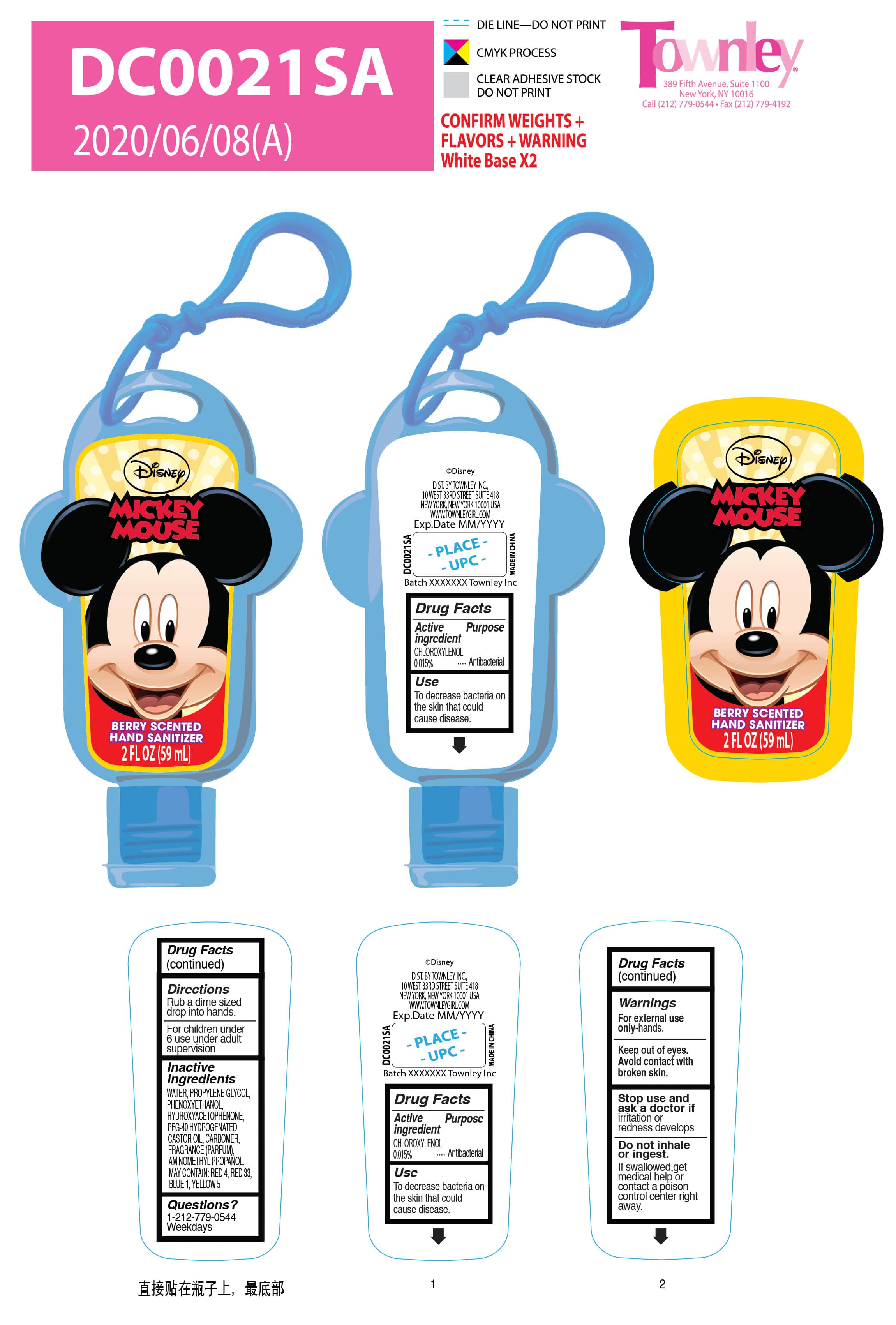 DRUG LABEL: DC berry scented hand sanitizer
NDC: 77901-001 | Form: LIQUID
Manufacturer: Foshan Astar Industry Co., Ltd
Category: otc | Type: HUMAN OTC DRUG LABEL
Date: 20200613

ACTIVE INGREDIENTS: CHLOROXYLENOL 0.015 g/100 mL
INACTIVE INGREDIENTS: FD&C BLUE NO. 1 0.0002 g/100 mL; HYDROXYACETOPHENONE 0.3 mL/100 mL; POLYOXYL 40 HYDROGENATED CASTOR OIL 0.3 mL/100 mL; BLACKBERRY 0.05 mL/100 mL; WATER 92.1996 mL/100 mL; CARBOMER 934 0.09 mL/100 mL; PROPYLENE GLYCOL 6.5 mL/100 mL; PHENOXYETHANOL 0.5 mL/100 mL; AMINOMETHYLPROPANOL 0.045 mL/100 mL

DC0021SA(blue, berry)

Active ingredient .............purpose

Chloroxylenol 0.015%..... Antibacterial

Use

To decrease bacteria on the skin that could cause disease.

Warnings

For external use only-hands

keep out of eyes- avoid contact with broken skin

Stop use and ask a dosctor if irritation or radness develops

Do not inhale or ingest. If swallowed, get medical help or contact a poison control right away.

Direction

Rub a dime sized drop into hands.

For children under 6 use under adult supervision

Inactive ingredients

INACTIVE INGREDIENTS: WATER, GLYCERIN, COCETH-7, PPG-1-PEG-9 LAURYL GLYCOL ETHER, CARBOMER, SODIUM HYDROXIDE, PEG-40 HYDROGENATED CASTOR OIL, FRAGRANCE (PARFUM).
MAY CONTAIN: RED 40, RED 33, BLUE 1, YELLOW 5.

Questions?

1-212-779-0544 weekdays